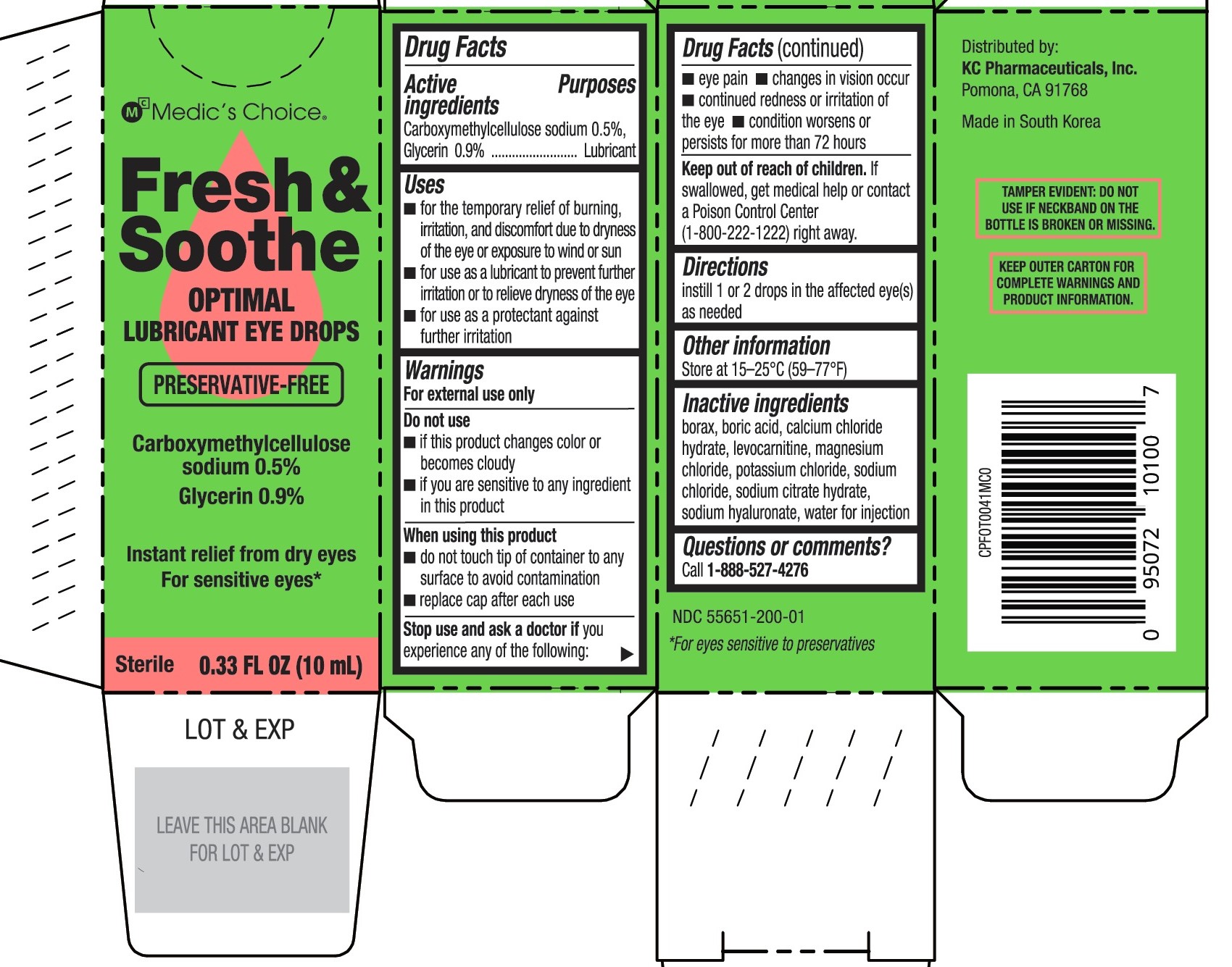 DRUG LABEL: Medics Choice Fresh and Soothe
NDC: 73669-200 | Form: SOLUTION/ DROPS
Manufacturer: Unimed
Category: otc | Type: HUMAN OTC DRUG LABEL
Date: 20250807

ACTIVE INGREDIENTS: CARBOXYMETHYLCELLULOSE SODIUM 5 mg/1 mL; GLYCERIN 9 mg/1 mL
INACTIVE INGREDIENTS: SODIUM HYALURONATE; SODIUM CHLORIDE; POTASSIUM CHLORIDE; SODIUM BORATE; BORIC ACID; WATER; LEVOCARNITINE; TRISODIUM CITRATE HYDRATE (2:11); CALCIUM CHLORIDE MONOHYDRATE; MAGNESIUM CHLORIDE

Medic's Choice Fresh & Soothe
Optimal Lubricant Eye Drops
(MFR for PLD Listing)

ACTIVE INGREDIENT

Carboxymethylcellulose sodium 0.5%

Glycerin 0.9%

PURPOSE

Eye Lubricant

INDICATIONS AND USAGE

- for the temporary relief of burning, irritation, and discomfort due to dryness of the eye or exposure to wind or sun
- for use as a lubricant to prevent further irritation or to relieve eye dryness
- may be used as a protectant against further irritation

Keep out of reach of children. If accidentally swallowed, get medical help or contact a Poison Control Center (1-800-222-1222) immediately.

Directions

- Instill 1 or 2 drops in the affected eye(s) as needed

INACTIVE INGREDIENT

borax, boric acid, calcium chloride hydrate, levocarnitine, magnesium chloride, potassium chloride, sodium chloride, sodium citrate hydrate, sodium hyaluronate, water

Warnings

For external use only

Do not use

if solution changes color or becomes cloudy
if you are sensitive or allergic to any ingredient in this product

When using this product

To avoid contamination, do not touch tip of container to any surface.
Replace cap after using.

Stop use and ask a doctor if you experience any of the following:

eye pain
changes in vision occur
redness or irritation of the eye(s) gets worse or lasts more than 72 hours